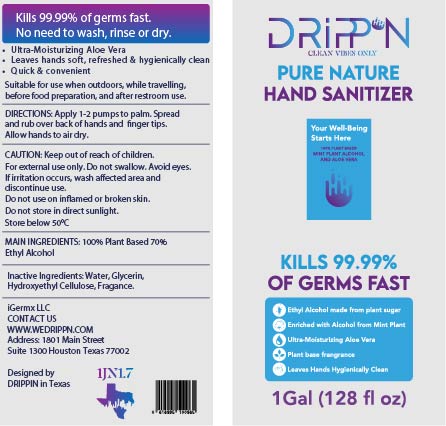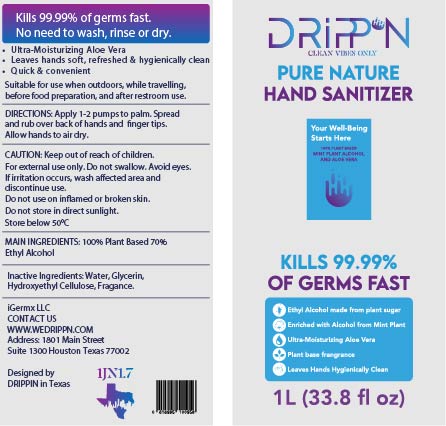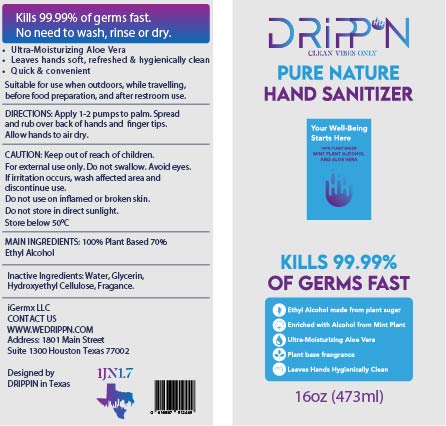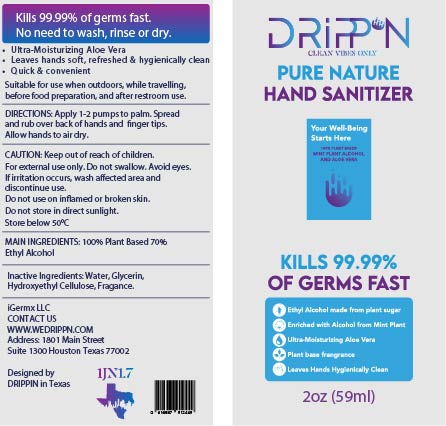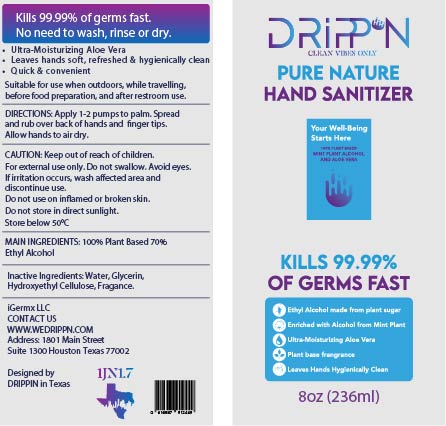 DRUG LABEL: Drippn Pure Nature Hand Sanitizer
NDC: 80740-003 | Form: GEL
Manufacturer: iGermx LLC
Category: otc | Type: HUMAN OTC DRUG LABEL
Date: 20200924

ACTIVE INGREDIENTS: ALCOHOL 0.7 mL/1 mL
INACTIVE INGREDIENTS: GLYCERIN 0.1854 mL/1 mL; ALOE VERA LEAF 0.5 mL/1 mL; CARBOMER HOMOPOLYMER, UNSPECIFIED TYPE 0.824 mL/1 mL; AMINOMETHYLPROPANOL 0.1524 mL/1 mL; PEPPERMINT OIL 0.215 mL/1 mL; WATER 0.37 mL/1 mL; MENTHOL 0.0515 mL/1 mL; FD&C BLUE NO. 1 0.00824 mL/1 mL

Hand Sanitizer

This is a hand sanitizer manufactured according to the Temporary Policy for Preparation of Certain Alcohol-Based Hand Sanitizer Products During the Public Health Emergency (CoViD-19); Guidance for Industry.

The hand sanitizer is manufactured using the following United States Pharmacopoeia (USP) grade ingredients in the preparation of the product (percentage in final product formulation) consistent with World Health Organization (WHO) recommendations:

1. Alcohol (ethanol) (USP or Food Chemical Codex (FCC) grade) (70%, volume/volume (v/v)) in an aqueous solution denatured according to Alcohol and Tobacco Tax and Trade Bureau regulations in 27 CFR part 20.
2. Glycerin 0.1854%
3. Hydrogen peroxide (0.125% v/v).
4. Water 36.95%
5. Carbopol 0.824%
6. Aloe Vera 0.515%
7. Peppermint 0.215%
8. AMP 0.1524%
9. Menthol 0.0515%
10. Blue 0.00824%

Active Ingredient(s)

Alcohol 70% v/v. Purpose: Antiseptic

Purpose

Antiseptic, Hand Sanitizer

Use

Hand Sanitizer to help reduce bacteria that potentially can cause disease. For use when soap and water are not available.

Warnings

For external use only. Flammable. Keep away from heat or flame

Do not use

- in children less than 2 months of age
- on open skin wounds

When using this product keep out of eyes, ears, and mouth. In case of contact with eyes, rinse eyes thoroughly with water.
Stop use and ask a doctor if irritation or rash occurs. These may be signs of a serious condition.
Keep out of reach of children. If swallowed, get medical help or contact a Poison Control Center right away.

Stop use and ask a doctor if irritation or rash occurs. These may be signs of a serious condition.

Keep out of reach of children. If swallowed, get medical help or contact a Poison Control Center right away.

Directions

- Place enough product on hands to cover all surfaces. Rub hands together until dry.
- Supervise children under 6 years of age when using this product to avoid swallowing.

Other information

- Store between 15-30C (59-86F)
- Avoid freezing and excessive heat above 40C (104F)

Inactive ingredients

Glycerin 0.1854%
Hydrogen peroxide (0.125% v/v).
Water 36.95%
Carbopol 0.824%
Aloe Vera 0.515%
Peppermint 0.215%
AMP 0.1524%
Menthol 0.0515%
Blue 0.00824%

Package Label - Principal Display Panel

80740-003-04 1 BOTTLE 236 ml

80740-003-01 1 BOTTLE 1 L

80740-003-02 1 BOTTLE 1 G

80740-003-03 1 BOTTLE 473 ml

80740-003-05 1 BOTTLE 59 ml